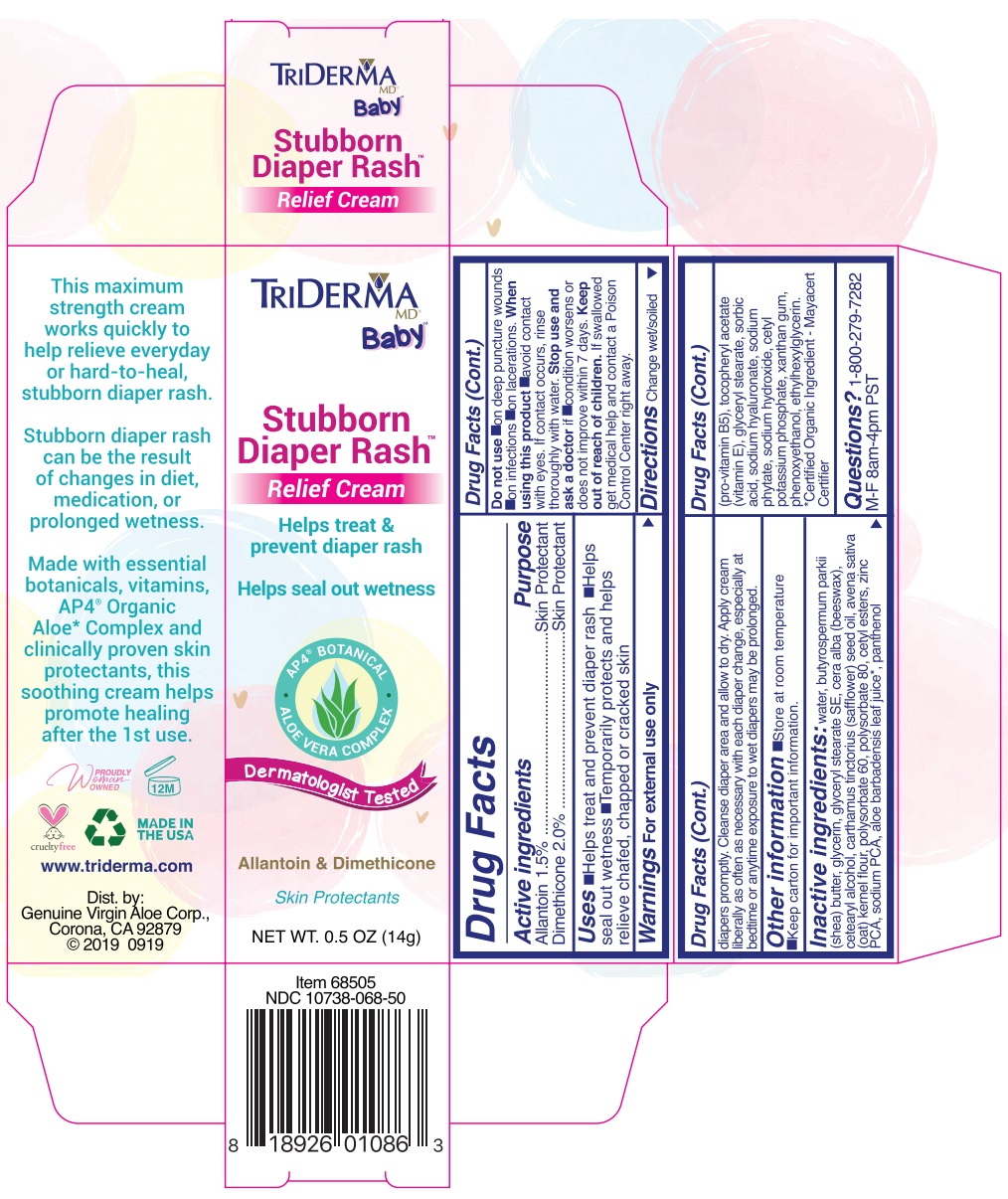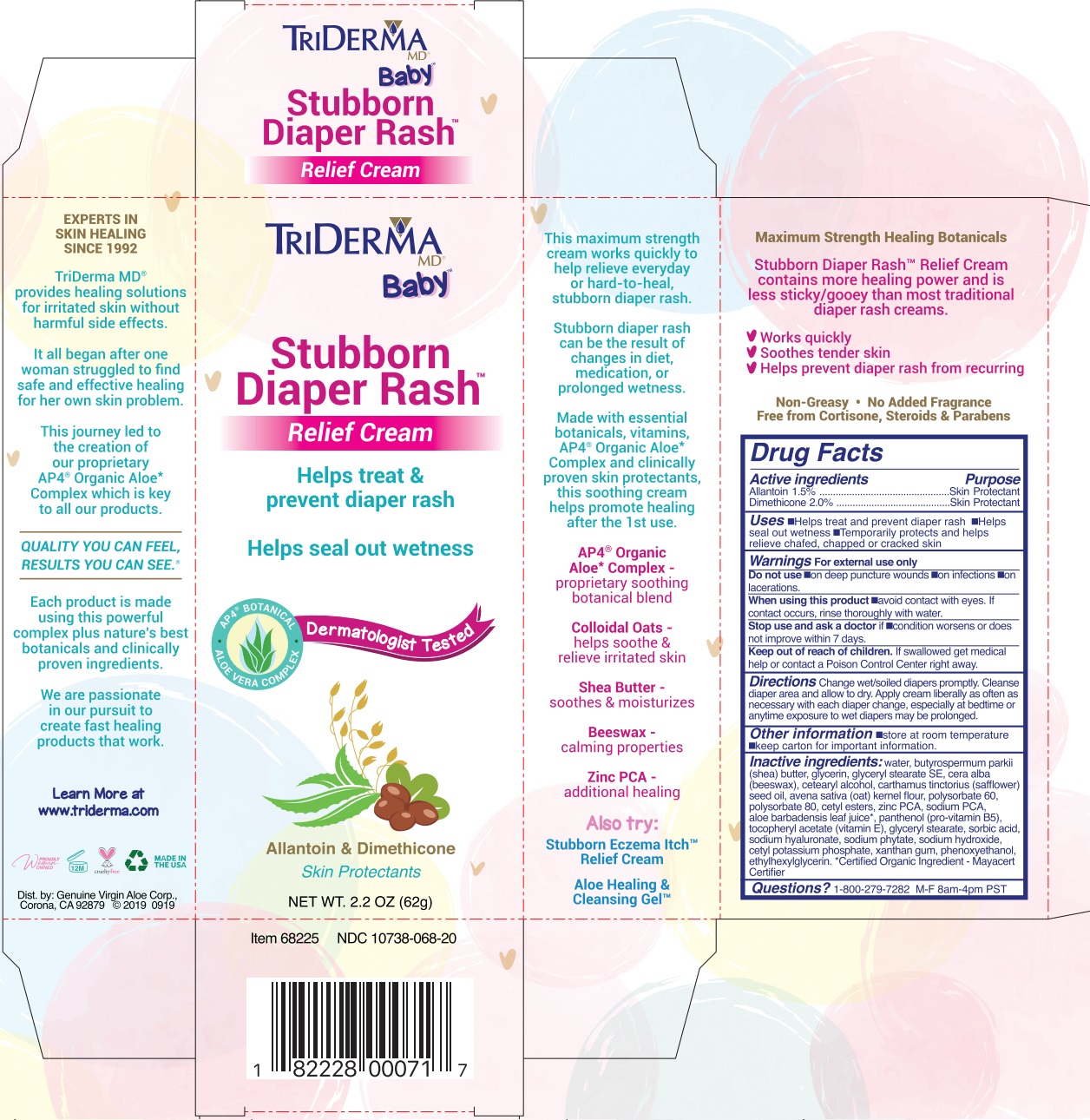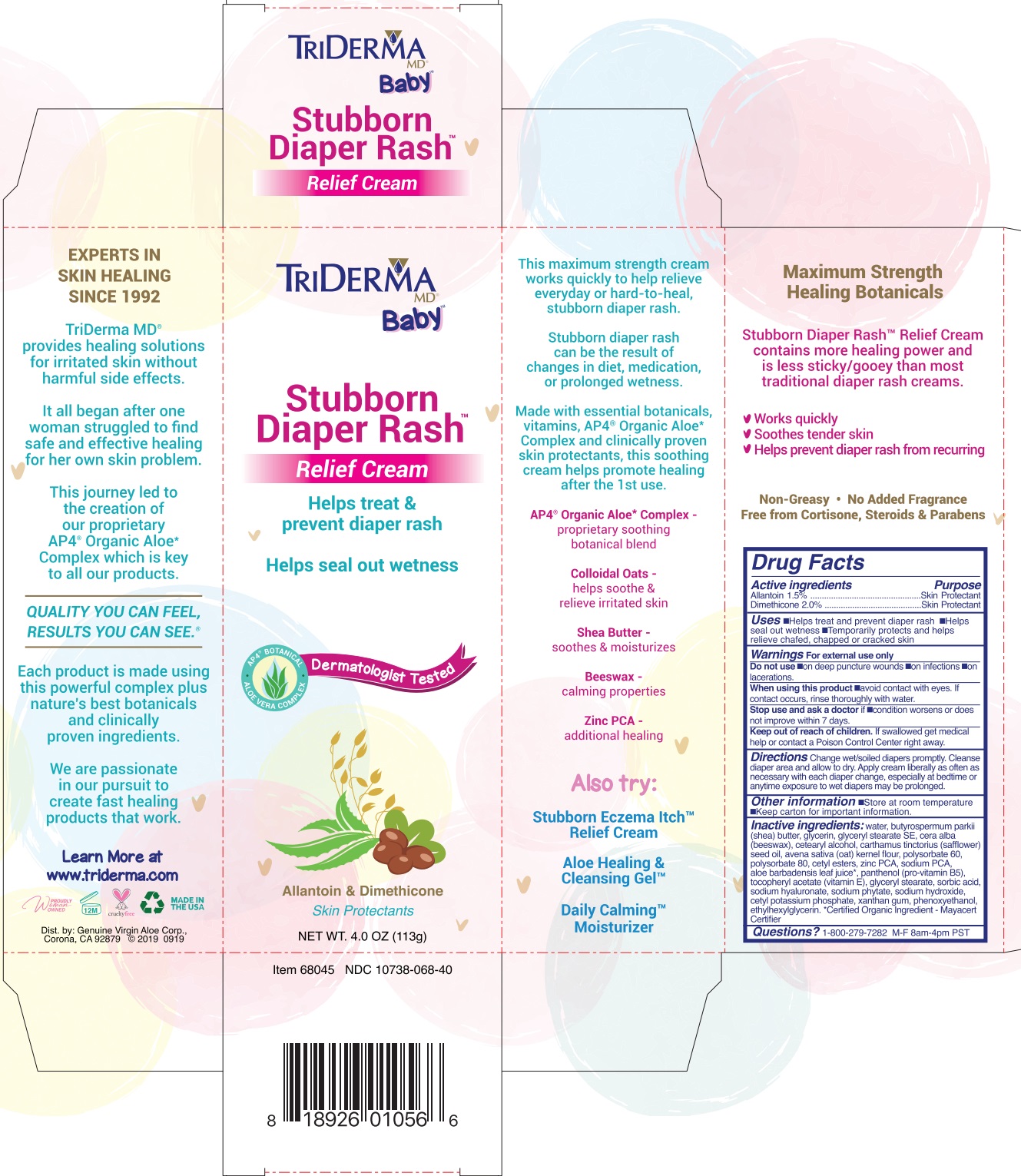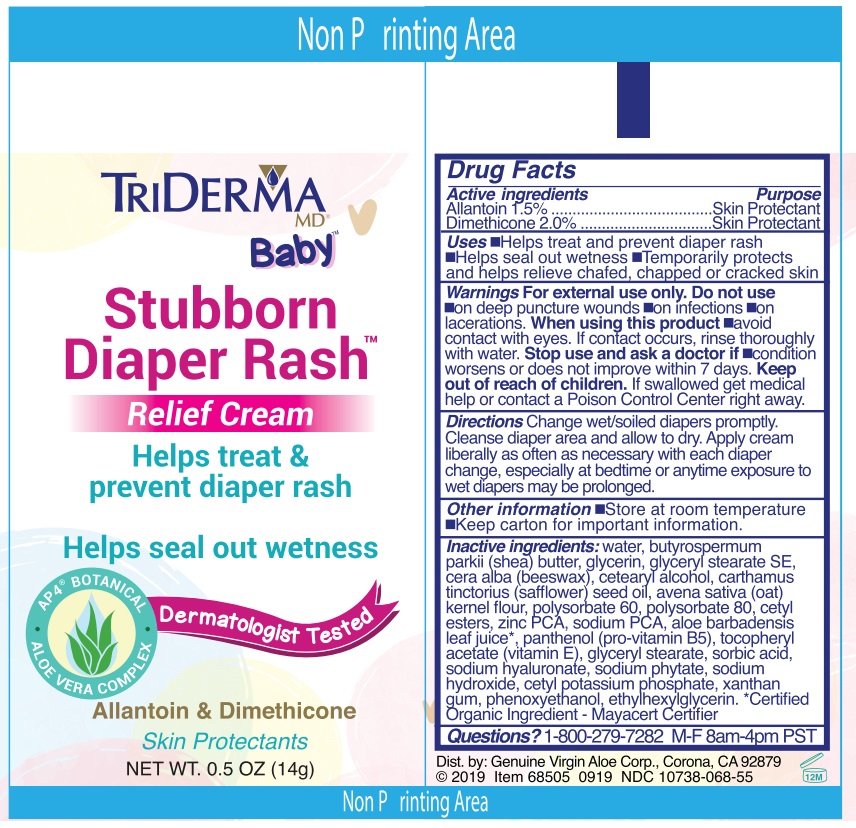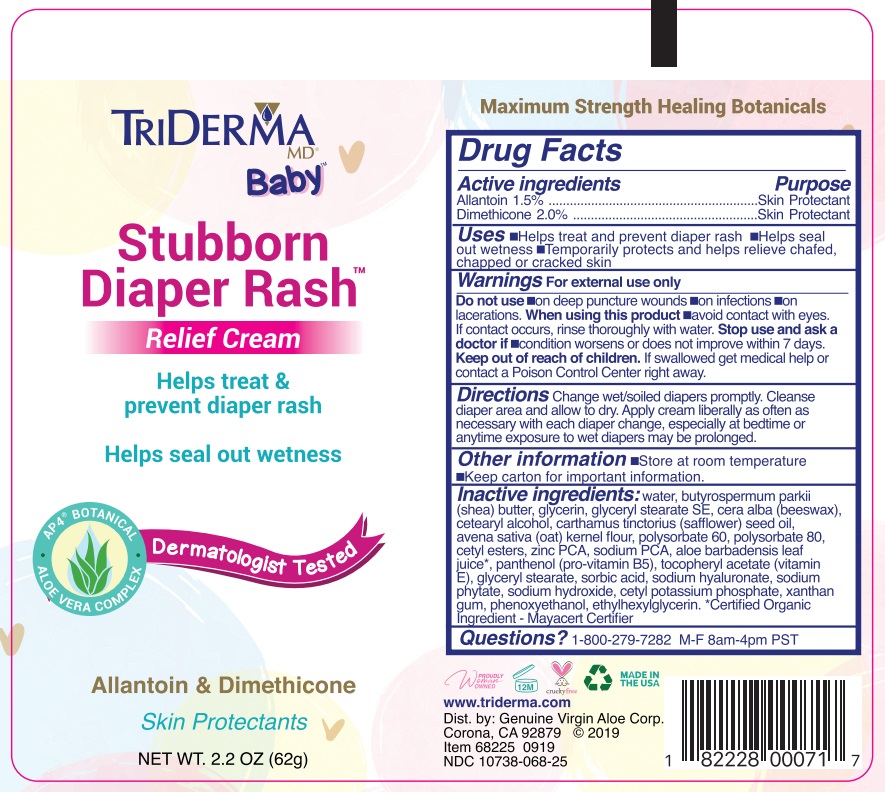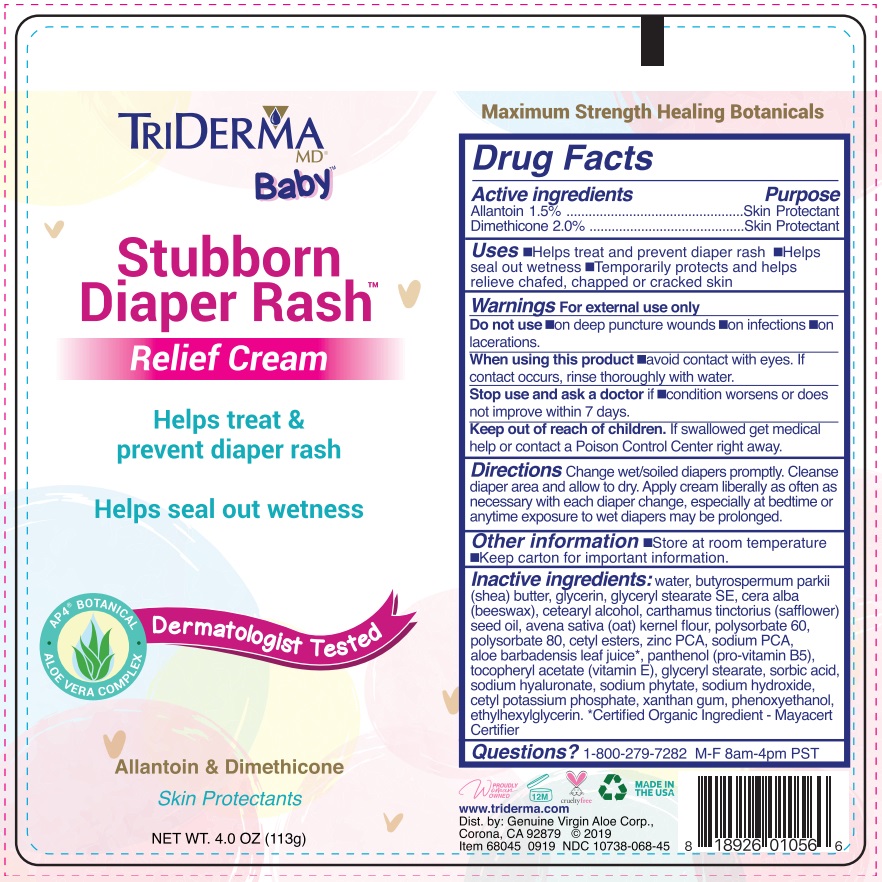 DRUG LABEL: TriDerma Stubborn Diaper Rash Relief
NDC: 10738-068 | Form: CREAM
Manufacturer: Genuine Virgin Aloe Corporation
Category: otc | Type: HUMAN OTC DRUG LABEL
Date: 20260128

ACTIVE INGREDIENTS: ALLANTOIN 1.5 g/100 g; DIMETHICONE 2 g/100 g
INACTIVE INGREDIENTS: WATER; SHEA BUTTER; GLYCERIN; GLYCERYL STEARATE SE; WHITE WAX; CETOSTEARYL ALCOHOL; SAFFLOWER OIL; OATMEAL; POLYSORBATE 60; POLYSORBATE 80; CETYL ESTERS WAX; ZINC PIDOLATE; SODIUM PYRROLIDONE CARBOXYLATE; ALOE VERA LEAF; DEXPANTHENOL; .ALPHA.-TOCOPHEROL ACETATE; GLYCERYL MONOSTEARATE; SORBIC ACID; HYALURONATE SODIUM; PHYTATE SODIUM; SODIUM HYDROXIDE; POTASSIUM PHOSPHATE, TRIBASIC; XANTHAN GUM; PHENOXYETHANOL; ETHYLHEXYLGLYCERIN

TRIDERMA Stubborn Diaper Rash™ Relief Cream

Active ingredients

Allantoin 1.5%
Dimethicone 2.0%

Purpose

Skin Protectant

INDICATIONS AND USAGE

Uses •Helps treat and prevent diaper rash •Helps seal out wetness •Temporarily protects and helps relieve chafed, chapped or cracked skin

Warnings For external use only

Do not use •on deep puncture wounds •on infections •on lacerations.

When using this product •avoid contact with eyes. If contact occurs, rinse thoroughly with water.

Stop use and ask a doctor if •condition worsens or does not improve within 7 days.

Keep out of reach of children. If swallowed get medical help or contact a Poison Control Center right away.

DOSAGE AND ADMINISTRATION

Directions Change wet/soiled diapers promptly. Cleanse diaper area and allow to dry. Apply cream liberally as often as necessary with each diaper change, especially at bedtime or anytime exposure to wet diapers may be prolonged.

Other information •Store at room temperature •Keep carton for important information.

INACTIVE INGREDIENT

Inactive ingredients: water, butyrospermum parkii (shea) butter, glycerin, glyceryl stearate SE, cera alba (beeswax), cetearyl alcohol, carthamus tinctorius (safflower) seed oil, avena sativa (oat) kernel flour, polysorbate 60, polysorbate 80, cetyl esters, zinc PCA, sodium PCA, aloe barbadensis leaf juice*, panthenol (pro-vitamin B5), tocopheryl acetate (vitamin E), glyceryl stearate, sorbic acid, sodium hyaluronate, sodium phytate, sodium hydroxide, cetyl potassium phosphate, xanthan gum, phenoxyethanol, ethylhexylglycerin. *Certified Organic Ingredient - Mayacert Certifier

QUESTIONS

Questions? 1-800-279-7282 M-F 8am-4pm PST

Helps treat & prevent diaper rash

Helps seal out wetness

Dermatologist Tested

This maximum strength cream works quickly to help relieve everyday or hard-to-heal, stubborn diaper rash.

Stubborn diaper rash can be result of changes in diet, medication, or prolonged wetness.

Made with essential botanicals, vitamins, AP4® Organic Aloe* Complex and clinically proven skin protectants, this soothing cream helps promote healing after the 1st use.

AP4® Organic Aloe* Complex - proprietary soothing botanical blend

Colloidal Oats - helps soothe & relieve irritated skin

Shea Butter - soothes & moisturizes

Beeswax - calming properties

Zinc PCA - additional healing

Also try:

Stubborn Eczema Itch™ Relief Cream

Aloe Healing & Cleansing Gel™

Daily Calming™ Moisturizer

Maximum Strength
Healing Botanicals

Stubborn Diaper Rash™ Relief Cream contains more healing power and is less sticky/gooey than most traditional diaper rash creams.

• Works quickly
• Soothes tender skin
• Helps prevent diaper rash from recurring

Non-Greasy • No Added Fragrance
Free from Cortisone, Steroids & Parabens

EXPERTS IN SKIN HEALING SINCE 1992

TriDerma MD® provides healing solutions for irritated skin without harmful side effects.

It all began after one woman struggled to find safe and effective healing for her own skin problem.

This journey led to the creation of our proprietary AP4® Organic Aloe* Complex which is key to all our products.

QUALITY YOU CAN FEEL, RESULTS YOU CAN SEE.®

Each product is made using this powerful complex plus nature’s best botanicals and clinically proven ingredients.

We are passionate in our pursuit to create fast healing products that work.

Learn More at www.triderma.com

MADE IN THE USA

Dist. by: Genuine Virgin Aloe Corp., Corona, CA 92879 ©2019 0919